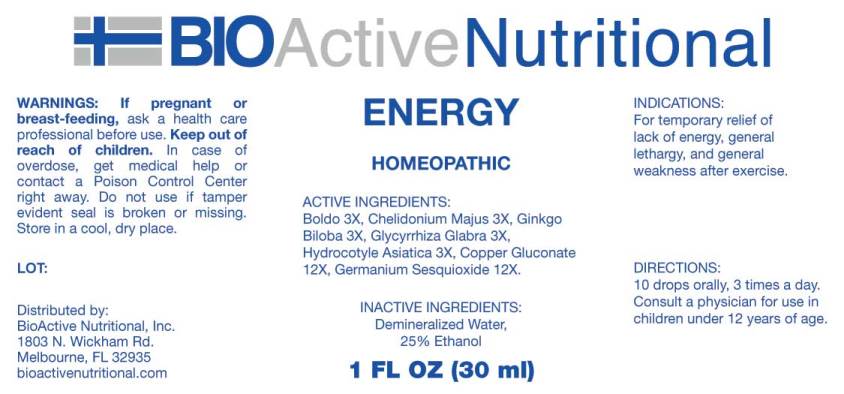 DRUG LABEL: Energy
NDC: 43857-0376 | Form: LIQUID
Manufacturer: BioActive Nutritional, Inc.
Category: homeopathic | Type: HUMAN OTC DRUG LABEL
Date: 20171129

ACTIVE INGREDIENTS: PEUMUS BOLDUS LEAF 3 [hp_X]/1 mL; CHELIDONIUM MAJUS 3 [hp_X]/1 mL; GINKGO 3 [hp_X]/1 mL; GLYCYRRHIZA GLABRA 3 [hp_X]/1 mL; CENTELLA ASIATICA 3 [hp_X]/1 mL; COPPER GLUCONATE 12 [hp_X]/1 mL; GERMANIUM SESQUIOXIDE 12 [hp_X]/1 mL
INACTIVE INGREDIENTS: WATER; ALCOHOL

Drug Facts:

ACTIVE INGREDIENTS:

Boldo 3X, Chelidonium Majus 3X, Ginkgo Biloba 3X, Glycyrrhiza Glabra 3X, Hydrocotyle Asiatica 3X, Copper Gluconate 12X, Germanium Sesquioxide 12X.

INDICATIONS:

For temporary relief of lack of energy, general lethargy, and general weakness after exercise.

WARNINGS:

If pregnant or breast-feeding, ask a health care professional before use.

Keep out of reach of children. In case of overdose, get medical help or contact a Poison Control Center right away.

Do not use if tamper evident seal is broken or missing.

Store in a cool, dry place.

Keep out of reach of children. In case of overdose, get medical help or contact a Poison Control Center right away.

DIRECTIONS:

10 drops orally, 3 times a day. Consult a physician for use in children under 12 years of age.

INDICATIONS:

For temporary relief of lack of energy, general lethargy, and general weakness after exercise.

INACTIVE INGREDIENTS:

Demineralized Water, 25% Ethanol.

QUESTIONS:

Distributed by:

BIOACTIVE NUTRITIONAL

Melbourne, FL 32935

For Nutritional Information write:

BioActive Nutritional, Inc.

1803 N. Wickham Rd.

Melbourne, FL 32935

PACKAGE LABEL DISPLAY:

BIOActive Nutritional

ENERGY

HOMEOPATHIC

1 FL OZ (30 ml)